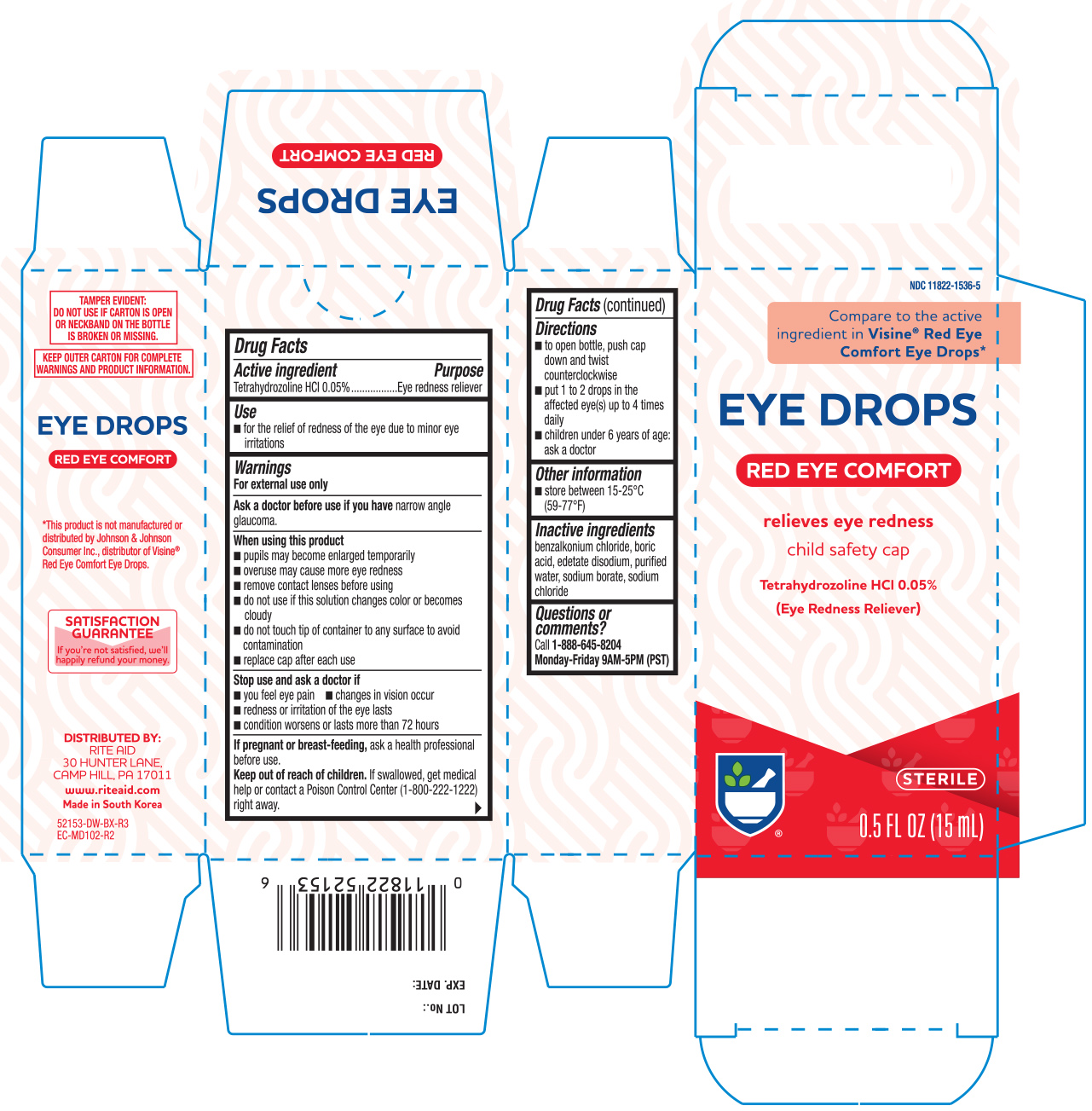 DRUG LABEL: Rite Aid Original Sterile Eye
NDC: 11822-1536 | Form: SOLUTION/ DROPS
Manufacturer: Rite Aid Corporation
Category: otc | Type: HUMAN OTC DRUG LABEL
Date: 20241220

ACTIVE INGREDIENTS: TETRAHYDROZOLINE HYDROCHLORIDE 0.5 mg/1 mL
INACTIVE INGREDIENTS: BENZALKONIUM CHLORIDE; BORIC ACID; EDETATE DISODIUM; WATER; SODIUM BORATE; SODIUM CHLORIDE

Rite Aid Eye Drops Fast-Acting (52153)

Active ingredient Purpose

Tetrahydrozoline HCl 0.05%...........Redness reliever

Use

- for the relief of redness of the eye due to minor eye irritations

Warnings

For external use only

Ask a doctor before use if you have

narrow angle glaucoma.

When using this product

- pupils may become enlarged temporarily
- overuse may cause more eye redness
- remove contact lenses before using
- do not use if this solution changes color or becomes cloudy
- do not touch tip of container to any surface to avoid contamination
- replace cap after each use

Stop use and ask a doctor if

- you feel eye pain
- changes in vision occur
- redness or irritation of the eye lasts
- condition worsens or alsts more than 72 hours

PREGNANCY OR BREAST FEEDING

If pregnant or breast-feeding, ask a health professional before use.

Keep out of reach of children. If swallowed, get medical help or contact a Poison Control Center right away.

Directions

- to open bottle, push cap down and twist counterclockwise. To close bottle, twist clockwise until it stops turning.
- put 1 to 2 drops in the affected eye(s) up to 4 times daily
- children under 6 years of age: ask a doctor

Other information

- store at 15° to 25°C (59° to 77°F)

Inactive ingredients

benzalkonium chloride, boric acid, edetate disodium, purified water, sodium borate, sodium chloride

DOSAGE AND ADMINISTRATION

DISTRIBUTED BY:

RITE AID

30 HUNTER LANE

CAMP HILL, PA 17011

MADE IN KOREA